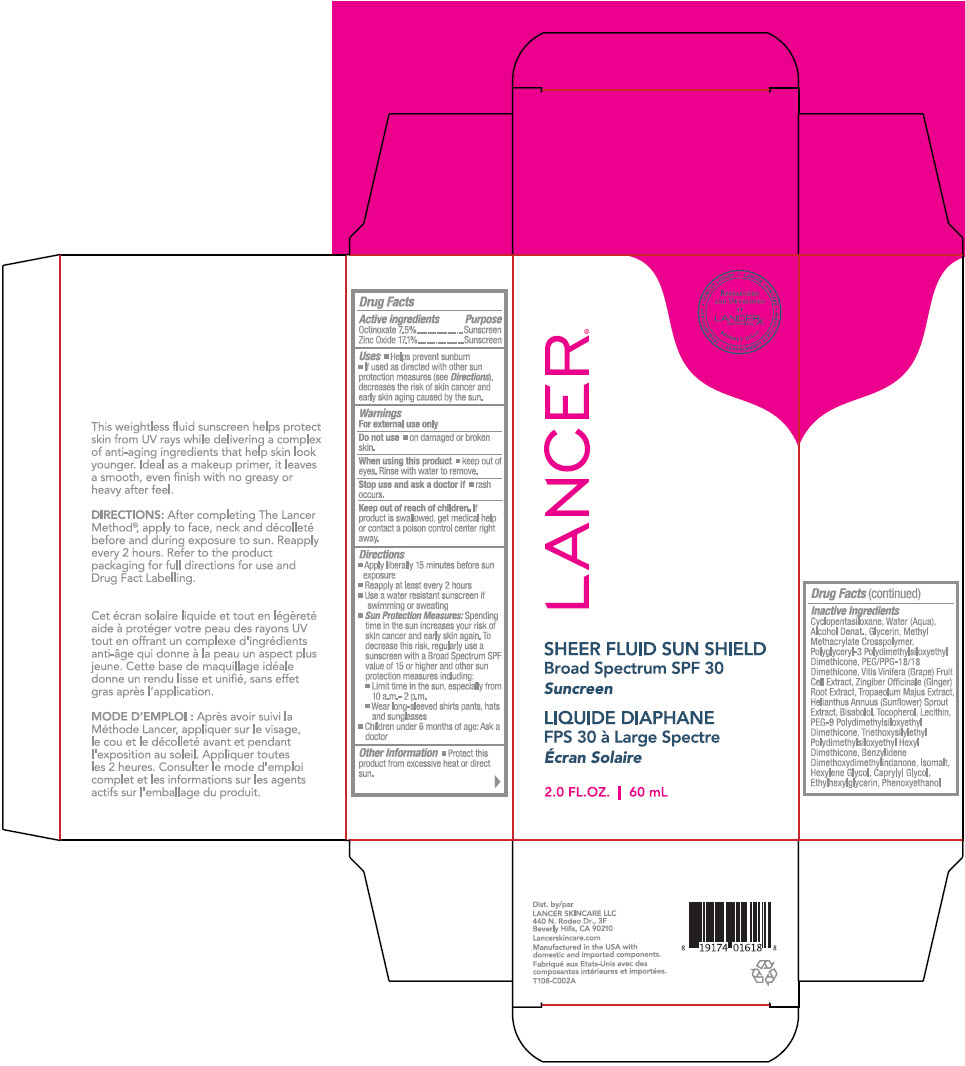 DRUG LABEL: Sheer Fluid Sun Shield 
NDC: 72704-108 | Form: LIQUID
Manufacturer: Lancer Skincare LLC.
Category: otc | Type: HUMAN OTC DRUG LABEL
Date: 20230119

ACTIVE INGREDIENTS: Octinoxate 7.5 g/100 mL; Zinc Oxide 17.1 g/100 mL
INACTIVE INGREDIENTS: Cyclomethicone 5; Water; Alcohol; Glycerin; METHYL METHACRYLATE/GLYCOL DIMETHACRYLATE CROSSPOLYMER; POLYGLYCERYL-3 POLYDIMETHYLSILOXYETHYL DIMETHICONE (4000 MPA.S); PEG/PPG-18/18 Dimethicone; Grape; Ginger; Tropaeolum Majus Whole; Helianthus Annuus Sprout; Levomenol; Tocopherol; PEG-9 Polydimethylsiloxyethyl Dimethicone; Triethoxysilylethyl Polydimethylsiloxyethyl Hexyl Dimethicone; Benzylidene Dimethoxydimethylindanone; Isomalt; Hexylene Glycol; Caprylyl Glycol; Ethylhexylglycerin; Phenoxyethanol; Lecithin, soybean

Sheer Fluid Sun Shield
Broad Spectrum SPF 30

Drug Facts

ACTIVE INGREDIENT

Active Ingredients | Purpose
Octinoxate 7.5% | Sunscreen
Zinc Oxide 17.1% | Sunscreen

Uses

- Helps prevent sunburn
- If used as directed with other sun protection measures (see Directions), decreases the risk of skin cancer and early skin aging caused by the sun.

Warnings

For external use only

Do not use

- on damaged or broken Skin.

When using this product

- keep out of eyes. Rinse with water to remove.

Stop use and ask a doctor if

- rash occurs.

Keep out of reach of children. If Product is swallowed, get medical help Or contact a poison control center right Away.

Directions

- Apply liberally 15 minutes before sun exposure
- Reapply at least every 2 hours
- Use a water resistant sunscreen if swimming or sweating
- Sun Protection Measures: Spending time in the sun increases your risk of skin cancer and early skin aging. To decrease this risk, regularly use a sunscreen with a Broad Spectrum SPF value of 15 or higher and other sun protection measures including:
  - Limit time in the sun, especially from 10 a.m.-2 p.m.
  - Wear long-sleeved shirts, pants, hats and sunglasses

- Children under 6 months of age: Ask a doctor

Other Information

- Protect this product from excessive heat or direct sun.

Inactive Ingredients

Cyclopentasiloxane, Water (Aqua), Alcohol Denat., Glycerin, Methyl Methacrylate Crosspolymer, Polyglyceryl-3 Polydimethylsiloxyethyl Dimethicone, PEG/PPG-18/18 Dimethicone, Vitis Vinifera (Grape) Fruit Cell Extract, Zingiber Officinale (Ginger) Root Extract, Tropaeolum Majus Extract, Helianthus Annuus (Sunflower) Sprout Extract, Bisabolol, Tocopherol, Lecithin, PEG-9 Polydimethylsiloxyethyl Dimethicone, Triethoxysilylethyl Polydimethylsiloxyethyl Hexyl Dimethicone, Benzylidene Dimethoxydimethylindanone, Isomalt, Hexylene Glycol, Caprylyl Glycol, Ethylhexylglycerin, Phenoxyethanol

Dist. by
LANCER SKINCARE LLC
440 N. Rodeo Dr., 3F
Beverly Hills, CA 90210

PRINCIPAL DISPLAY PANEL - 60 mL Bottle Carton

LANCER®

• UTMOST LUXURY
• LANCER SKINCARE
• FIRST-CLASS DERMATOLOGY
• TRUE EFFICACY

RESEARCHED
AND DEVELOPED
AT
LANCERX™
dermatology
BEVERLY HILLS

SHEER FLUID SUN SHIELD
Broad Spectrum SPF 30
Suncreen

2.0 FL.OZ. | 60 mL